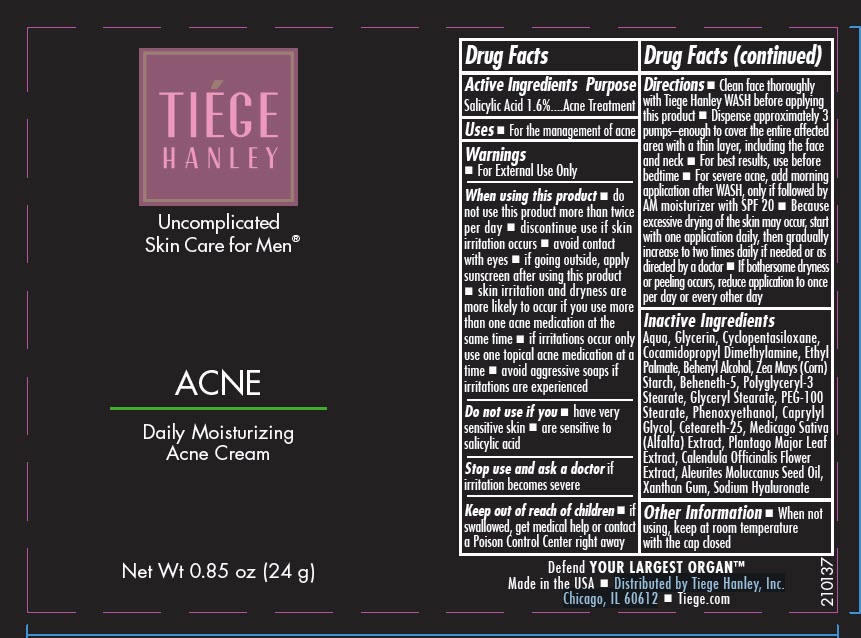 DRUG LABEL: Tiege Hanley Daily Moisturizing Acne
NDC: 71714-002 | Form: CREAM
Manufacturer: TIEGE HANLEY,Inc.
Category: otc | Type: HUMAN OTC DRUG LABEL
Date: 20230320

ACTIVE INGREDIENTS: SALICYLIC ACID 16 mg/1 g
INACTIVE INGREDIENTS: WATER; STARCH, CORN; XANTHAN GUM; GLYCERIN; POLYGLYCERYL-3 STEARATE; BEHENETH-5; GLYCERYL MONOSTEARATE; PEG-100 STEARATE; CETEARETH-25; ETHYL PALMATE; DOCOSANOL; CYCLOMETHICONE 5; ALFALFA TOP; PLANTAGO MAJOR LEAF; CALENDULA OFFICINALIS FLOWER; HYALURONATE SODIUM; PHENOXYETHANOL; CAPRYLYL GLYCOL; KUKUI NUT OIL; COCAMIDOPROPYL DIMETHYLAMINE

Tiége Hanley Daily Moisturizing Acne Cream

Drug Facts

Active Ingredients

Salicylic Acid 1.6%

Purpose

Acne Treatment

Uses

- For the management of acne

Warnings

- For External Use Only

When using this product

- do not use this product more than twice per day
- discontinue use if skin irritation occurs
- avoid contact with eyes
- if going outside, apply sunscreen after using this product
- skin irritation and dryness are more likely to occur if you use more than one acne medication at the same time
- if irritations occur only use one topical acne medication at a time
- avoid aggressive soaps if irritations are experienced

Do not use if you

- have very sensitive skin
- are sensitive to salicylic acid

Stop use and ask a doctor if irritation becomes severe

Keep out of reach of children

- if swallowed, get medical help or contact a Poison Control Center right away

Directions

- Clean face thoroughly with Tiege Hanley WASH before applying this product
- Dispense approximately 3 pumps–enough to cover the entire affected area with a thin layer, including the face and neck
- For best results, use before bedtime
- For severe acne, add morning application after WASH, only if followed by AM moisturizer with SPF 20
- Because excessive drying of the skin may occur, start with one application daily, then gradually increase to two times daily if needed or as directed by a doctor
- If bothersome dryness or peeling occurs, reduce application to once per day or every other day

Inactive Ingredients

Aqua, Glycerin, Cyclopentasiloxane, Cocamidopropyl Dimethylamine, Ethyl Palmate, Behenyl Alcohol, Zea Mays (Corn) Starch, Beheneth-5, Polyglyceryl-3 Stearate, Glyceryl Stearate, PEG-100 Stearate, Phenoxyethanol, Caprylyl Glycol, Ceteareth-25, Medicago Sativa (Alfalfa) Extract, Plantago Major Leaf Extract, Calendula Officinalis Flower Extract, Aleurites Moluccanus Seed Oil, Xanthan Gum, Sodium Hyaluronate

Other Information

- When not using, keep at room temperature with the cap closed

- Distributed by Tiege Hanley, Inc.
  Chicago, IL 60612

PRINCIPAL DISPLAY PANEL - 24 g Bottle Label

TIÉGE
HANLEY

Uncomplicated
Skin Care for Men®

ACNE

Daily Moisturizing
Acne Cream

Net Wt 0.85 oz (24 g)